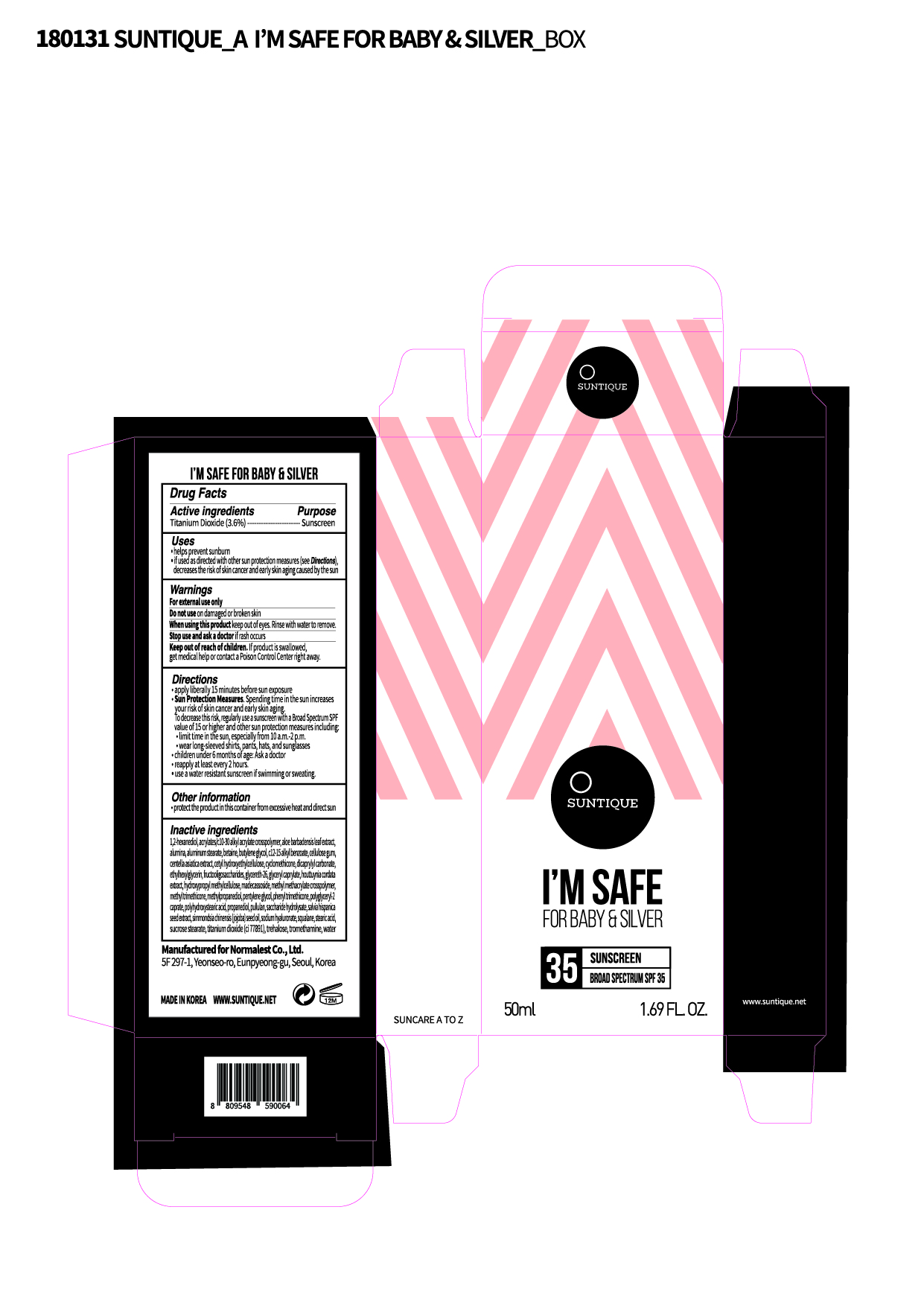 DRUG LABEL: IM SAFE FOR BABY AND SILVER
NDC: 72284-0005 | Form: LOTION
Manufacturer: Normalest Co., Ltd.
Category: otc | Type: HUMAN OTC DRUG LABEL
Date: 20190306

ACTIVE INGREDIENTS: TITANIUM DIOXIDE 1.78 g/50 mL
INACTIVE INGREDIENTS: DICAPRYLYL CARBONATE; METHYLPROPANEDIOL; CYCLOMETHICONE; SALVIA HISPANICA SEED; FOSFRUCTOSE; SIMMONDSIA CHINENSIS SEED; CARBOXYMETHYLCELLULOSE SODIUM; TROMETHAMINE; BETAINE; GLYCERYL CAPRYLATE; SQUALANE; BUTYLENE GLYCOL; PENTYLENE GLYCOL; MADECASSOSIDE; INVERT SUGAR; PHENYL TRIMETHICONE; 1,2-HEXANEDIOL; SUCROSE STEARATE; TREHALOSE; PULLULAN; HYALURONATE SODIUM; PROPANEDIOL; HYPROMELLOSES; STEARIC ACID; ALKYL (C12-15) BENZOATE; POLYHYDROXYSTEARIC ACID (2300 MW); WATER; GLYCERETH-26; METHYL TRIMETHICONE; CENTELLA ASIATICA; HOUTTUYNIA CORDATA WHOLE; METHYL METHACRYLATE/GLYCOL DIMETHACRYLATE CROSSPOLYMER; ETHYLHEXYLGLYCERIN; ALUMINUM STEARATE

PACKAGE LABEL

Active Ingredient

Titamin Dioxide 3.57 %

Inactive Ingredients

Water, Propanediol, Phenyl Trimethicone, Dicaprylyl Carbonate, Methylpropanediol, Cyclomethicone, 1,2-Hexanediol, Glycereth-26, Methyl Trimethicone, Salvia Hispanica Seed Extract, Centella Asiatica Extract, Houttuynia Cordata Extract, Polyglyceryl-2 Caprate, Methyl Methacrylate Crosspolymer, Sucrose Stearate, Fructooligosaccharides, Saccharide Hydrolysate, Simmondsia Chinensis (Jojoba) Seed Oil, Acrylates/C10-30 Alkyl Acrylate Crosspolymer, Cellulose Gum, Tromethamine, Hydroxypropyl Methylcellulose, Cetyl Hydroxyethylcellulose, Stearic Acid, Alumina, Betaine, Trehalose, Pullulan, Glyceryl Caprylate, Ethylhexylglycerin, Squalane, Butylene Glycol, Pentylene Glycol, Aloe Barbadensis Leaf Extract, Madecassoside, C12-15 Alkyl Benzoate, Sodium Hyaluronate, Aluminum Stearate, Polyhydroxystearic Acid